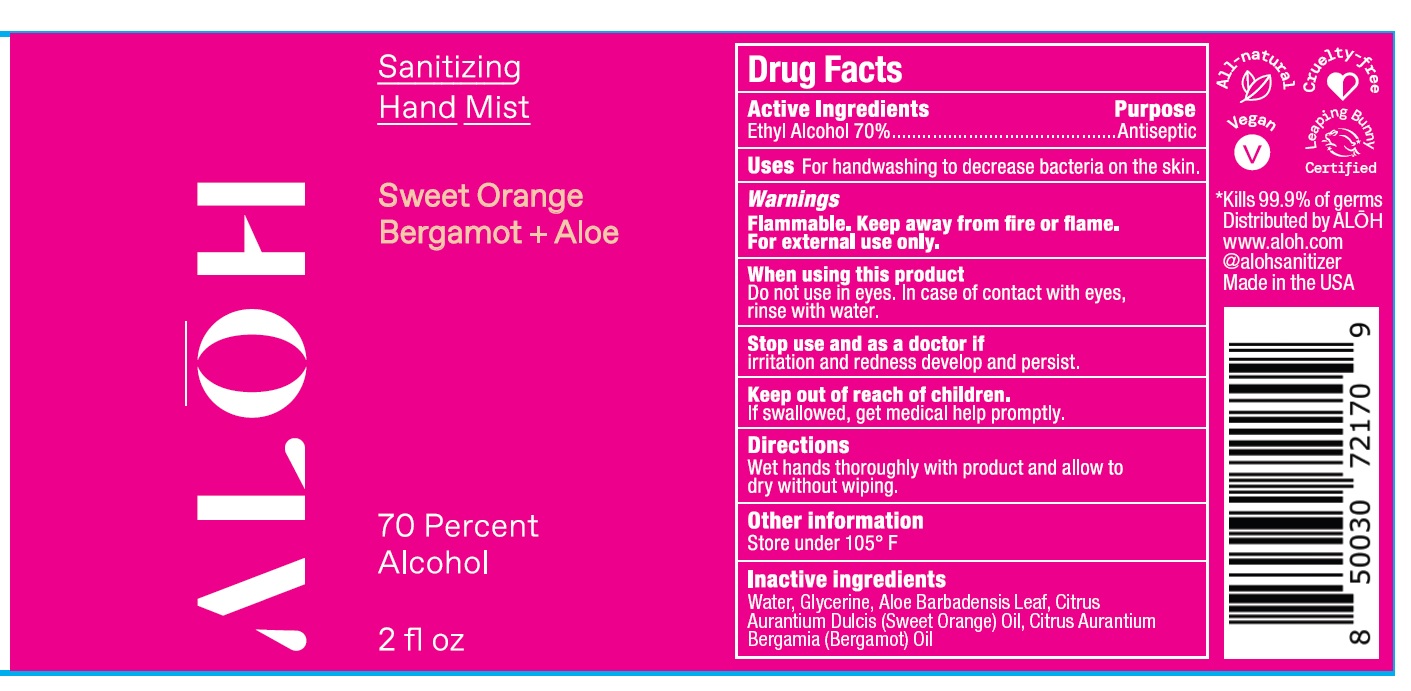 DRUG LABEL: Sanitizing Hand Mist
NDC: 82355-001 | Form: SPRAY
Manufacturer: ALO New York LLC
Category: otc | Type: HUMAN OTC DRUG LABEL
Date: 20250401

ACTIVE INGREDIENTS: ALCOHOL 70 mL/100 mL
INACTIVE INGREDIENTS: ORANGE OIL, COLD PRESSED; WATER; GLYCERIN; ALOE BARBADENSIS LEAF; CITRUS AURANTIUM BERGAMIA (BERGAMOT) LEAF OIL

ALO Brands Hand Sanitzer

Active ingredients

Ethyl Alcohol

Purpose

Antiseptic

Uses

For handwashing to decrease bacteria on the skin

Warnings

Flammable. Keep away from fire or flame. For external use only.

When using this product

Do not use in eyes. In case of contact with eyes, rinse with water.

Stop use and ask doctor if

irritation and redness develop and persist.

Keep out of reach of chidren.

If swallowed, get medical help promptly.

Directions

Wet hands thoroughly with product and allow to dry without wiping.

Other information

Store under 105°F

Inactive Ingredients

Water, Glycerine, Aloe Barbadensis Leaf, Citrus Aurantium Dulcis (Sweet Orange) Oil, Citrus Aurantium Bergamia (Bergamot) Oil

Sanitizing Hand Gel - Unscented + Aloe NDC 82355-020-08

NDC 82355-001-02

ALOH Sanitizing Hand Mist

Sweet Orange Bergamot + Aloe

70 Percent Alcohol

2 fl oz